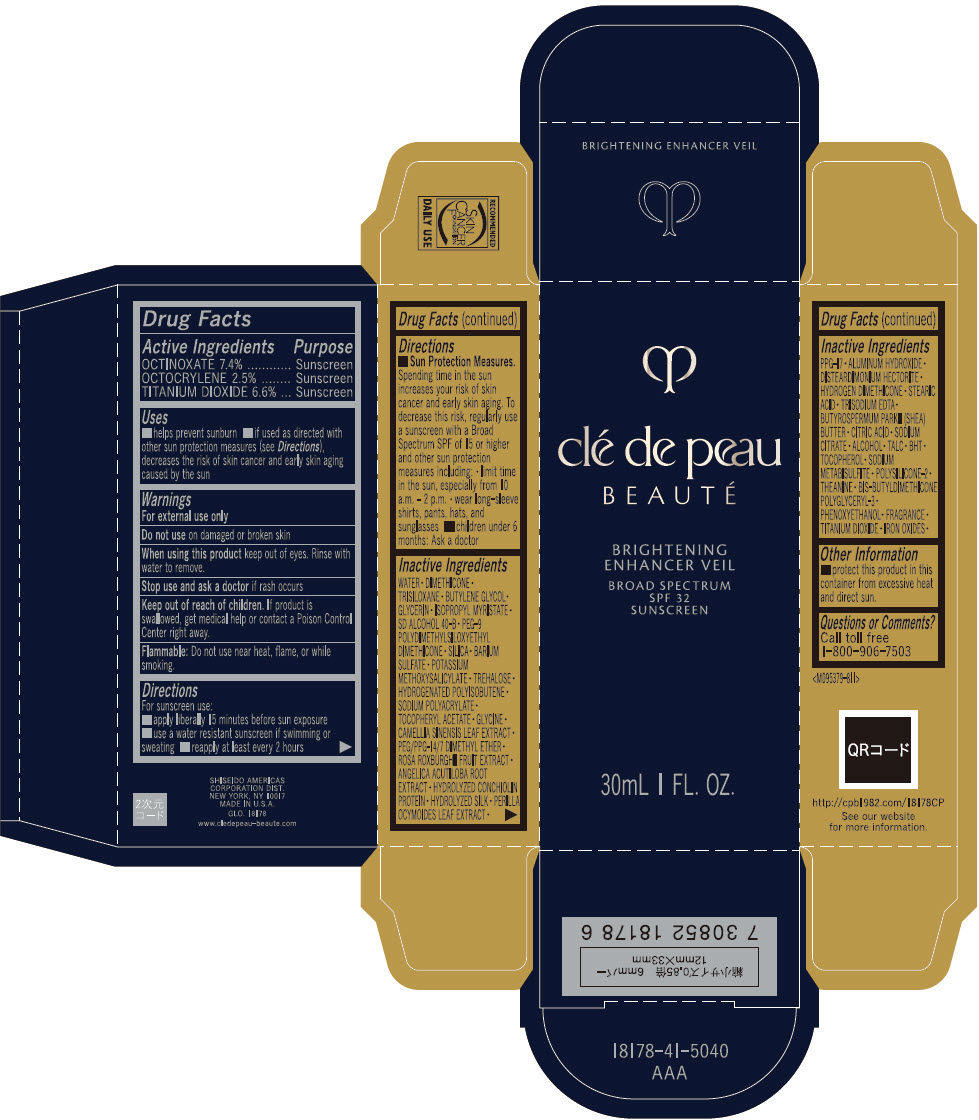 DRUG LABEL: cle de peau BEAUTE BRIGHTENING ENHANCER VEIL
NDC: 58411-838 | Form: EMULSION
Manufacturer: SHISEIDO AMERICAS CORPORATION
Category: otc | Type: HUMAN OTC DRUG LABEL
Date: 20260105

ACTIVE INGREDIENTS: OCTINOXATE 2220 mg/30 mL; OCTOCRYLENE 750 mg/30 mL; TITANIUM DIOXIDE 1980 mg/30 mL
INACTIVE INGREDIENTS: WATER; DIMETHICONE; TRISILOXANE; BUTYLENE GLYCOL; GLYCERIN; ISOPROPYL MYRISTATE; LAURYL PEG-9 POLYDIMETHYLSILOXYETHYL DIMETHICONE; SILICON DIOXIDE; BARIUM SULFATE; POTASSIUM METHOXYSALICYLATE; TREHALOSE; .ALPHA.-TOCOPHEROL ACETATE; GLYCINE; GREEN TEA LEAF; PEG/PPG-14/7 DIMETHYL ETHER; ROSA ROXBURGHII FRUIT; ANGELICA ACUTILOBA ROOT; PERILLA FRUTESCENS LEAF; PPG-17; ALUMINUM HYDROXIDE; DISTEARDIMONIUM HECTORITE; STEARIC ACID; EDETATE TRISODIUM; SHEA BUTTER; CITRIC ACID MONOHYDRATE; SODIUM CITRATE, UNSPECIFIED FORM; ALCOHOL; TALC; BUTYLATED HYDROXYTOLUENE; TOCOPHEROL; SODIUM METABISULFITE; THEANINE; PHENOXYETHANOL; FERRIC OXIDE RED

clé de peau BEAUTÉ BRIGHTENING ENHANCER VEIL

Drug Facts

ACTIVE INGREDIENT

Active ingredients | Purpose
Octinoxate 7.4% | Sunscreen
Octocrylene 2.5% | Sunscreen
Titanium Dioxide 6.6% | Sunscreen

Uses

- helps prevent sunburn
- if used as directed with other sun protection measures (see Directions), decreases the risk of skin cancer and early skin aging caused by the sun

Warnings

For external use only

Do not use ondamaged or broken skin

WHEN USING

When using this productkeep out of eyes. Rinse with water to remove.

Stop useand ask a doctor if rash occurs.

Keep out of reach of children.If product is swallowed, get medical help or contact a Poison Control Center right away.

Flammable:Do not use near heat, flame, or while smoking.

Directions

For sunscreen use:

- apply liberally 15 minutes before sun exposure
- use a water resistant sunscreen if swimming or sweating
- reapply at least every 2 hours
- Sun Protection Measures. Spending time in the sun increases your risk of skin cancer and early skin aging. To decrease this risk, regularly use a sunscreen with a broad spectrum SPF value of 15 or higher and other sun protection measures including:
  - limit time in the sun, especially from 10 a.m. – 2 p.m.
  - wear long-sleeve shirts, pants, hats, and sunglasses
- children under 6 months: Ask a doctor

Inactive Ingredients

WATER•DIMETHICONE•TRISILOXANE•BUTYLENE GLYCOL•GLYCERIN•ISOPROPYL MYRISTATE•SD ALCOHOL 40-B•PEG-9 POLYDIMETHYLSILOXYETHYL DIMETHICONE•SILICA•BARIUM SULFATE•POTASSIUM METHOXYSALICYLATE•TREHALOSE•HYDROGENATED POLYISOBUTENE•SODIUM POLYACRYLATE•TOCOPHERYL ACETATE•GLYCINE•CAMELLIA SINENSIS LEAF EXTRACT•PEG/PPG-14/7 DIMETHYL ETHER•ROSA ROXBURGHII FRUIT EXTRACT•ANGELICA ACUTILOBA ROOT EXTRACT•HYDROLYZED CONCHIOLIN PROTEIN•HYDROLYZED SILK•PERILLA OCYMOIDES LEAF EXTRACT•PPG-17•ALUMINUM HYDROXIDE•DISTEARDIMONIUM HECTORITE•HYDROGEN DIMETHICONE•STEARIC ACID•TRISODIUM EDTA•BUTYROSPERMUM PARKII (SHEA) BUTTER•CITRIC ACID•SODIUM CITRATE•ALCOHOL•TALC•BHT•TOCOPHEROL•SODIUM METABISULFITE•POLYSILICONE-2•THEANINE•BIS-BUTYLDIMETHICONE POLYGLYCERYL-3•PHENOXYETHANOL•FRAGRANCE•TITANIUM DIOXIDE•IRON OXIDES•

Other information

- protect this product in this container from excessive heat and direct sun.

Questions or comments?

Call toll free 1-800-906-7503

PRINCIPAL DISPLAY PANEL - 30 mL Bottle Box

clé de peau
BEAUTÉ

BRIGHTENING
ENHANCER VEIL

BROAD SPECTRUM
SPF 32
SUNSCREEN

30mL 1 FL. OZ.